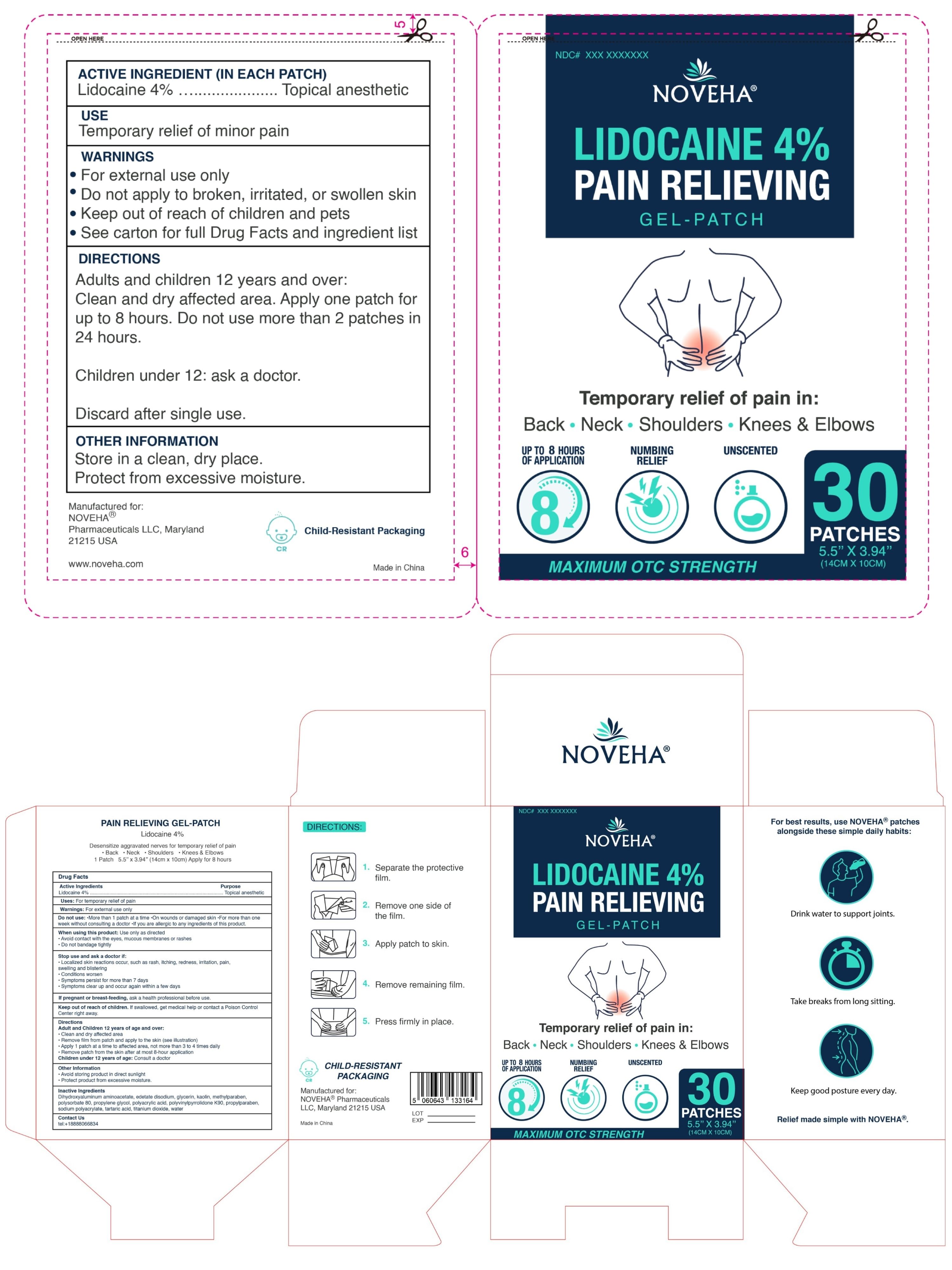 DRUG LABEL: Pain Relieveing Gel-Patch
NDC: 84008-001 | Form: PATCH
Manufacturer: Bullet point LLC
Category: otc | Type: HUMAN OTC DRUG LABEL
Date: 20251023

ACTIVE INGREDIENTS: LIDOCAINE 0.04 g/1 g
INACTIVE INGREDIENTS: PROPYLPARABEN; WATER; POLYSORBATE 80; DIHYDROXYALUMINUM AMINOACETATE ANHYDROUS; TARTARIC ACID; METHYLPARABEN; TITANIUM DIOXIDE; SODIUM POLYACRYLATE (2500000 MW); POVIDONE K90; POLYACRYLIC ACID (250000 MW); GLYCERIN; KAOLIN; PROPYLENE GLYCOL

DOSAGE AND ADMINISTRATION

Adults and children 12 years old and over:

- Clean and dry the affected area.
- Apply 1 patch to the affected area.
- Do not exceed 1 patch at a time.
- Leave in place for up to 8 hours.
- Do not use more than 1 patch in 24 hours unless directed by a doctor.
  Children under 12 years old: ask a doctor.

WARNINGS

For external use only

INACTIVE INGREDIENT

Dihydroxyaluminum Aminoacetate, Glycerin, Kaolin, Methylparaben, Polysorbate 80, Propylene Glycol, Polyacrylic Acid, Polyvinylpyrrolidone K90, Propylparaben, Sodium Polyacrylate, Tartaric Acid, Titanium Dioxide, Water

INDICATIONS AND USAGE

For temporary relief of pain.

Keep out of reach of children. If swallowed, get medical help or contact Poison Control.

PURPOSE

Topical anesthetic.